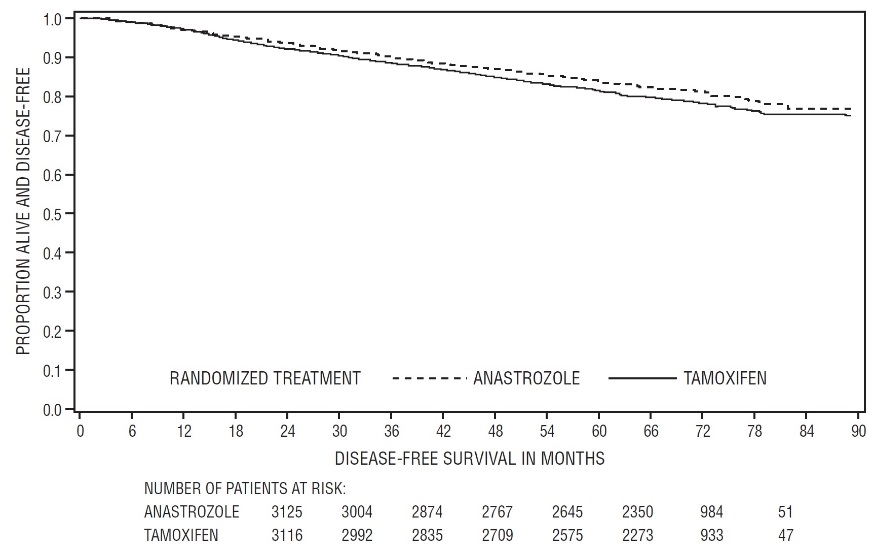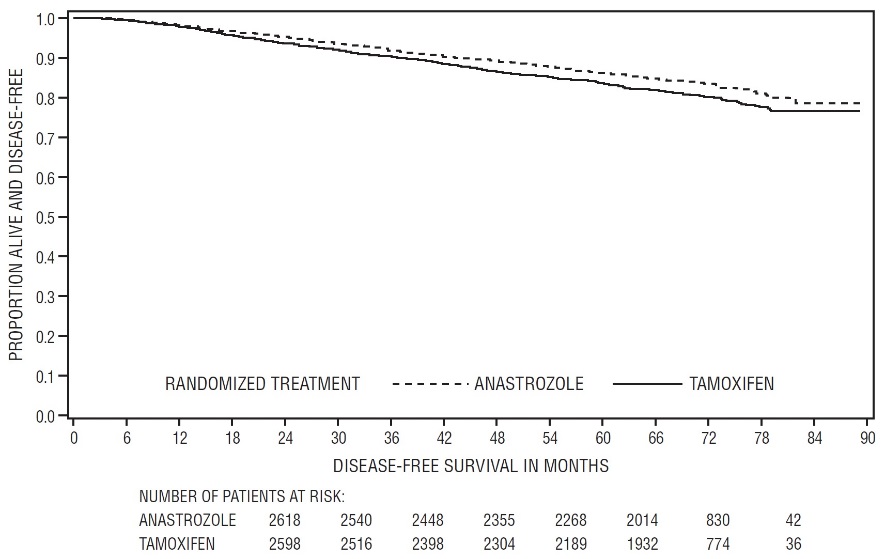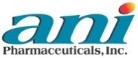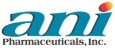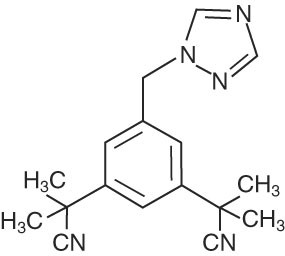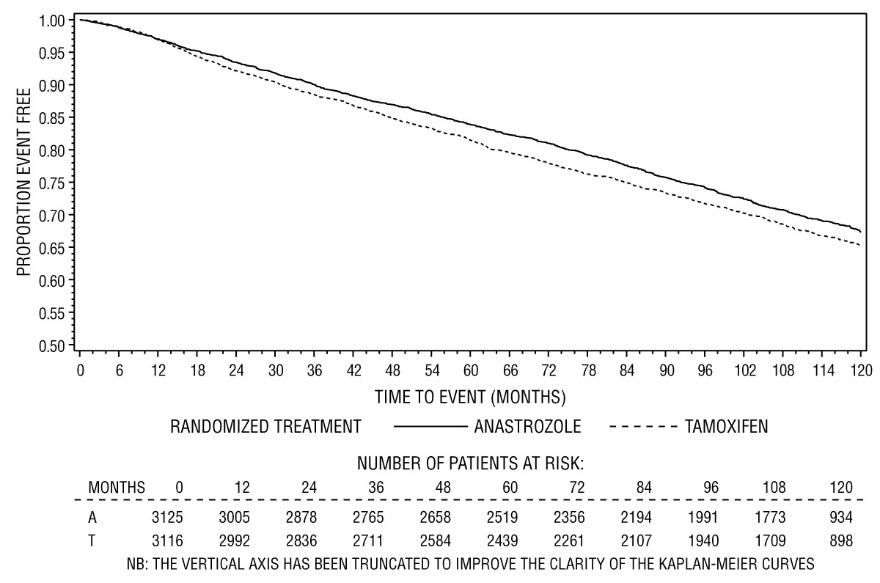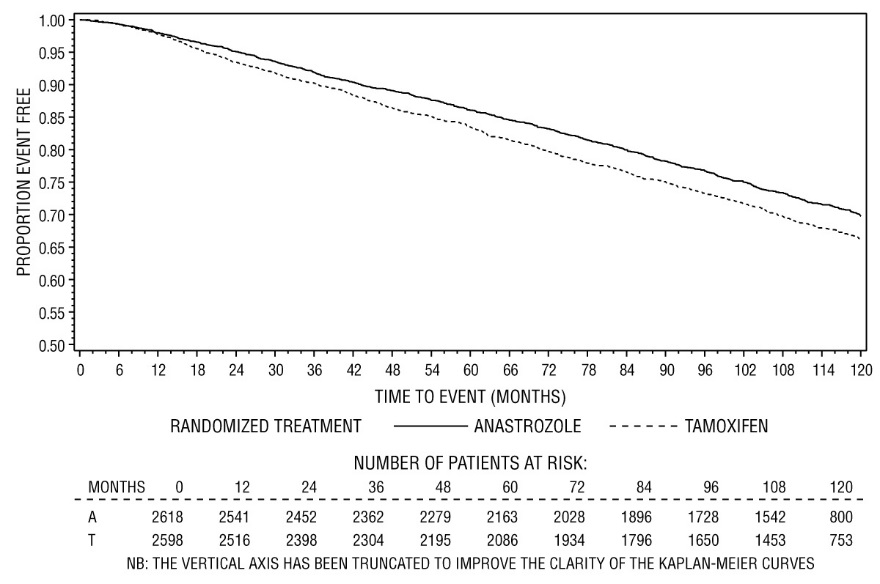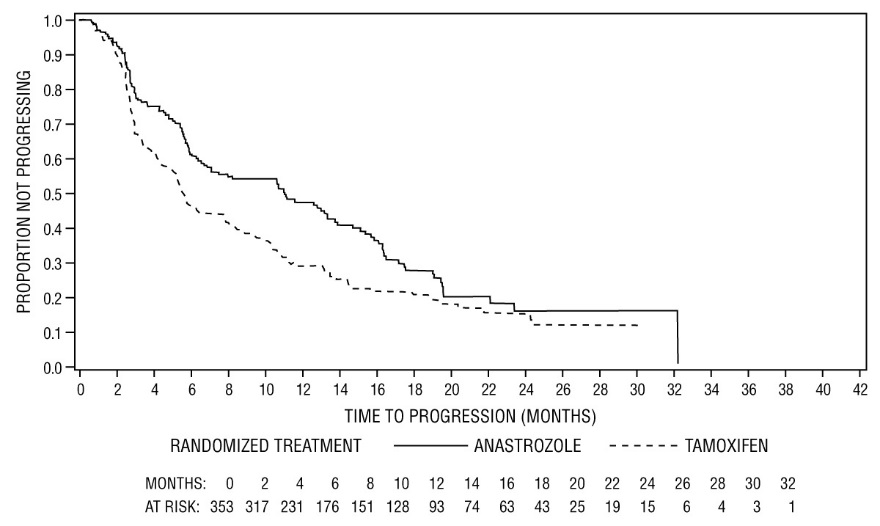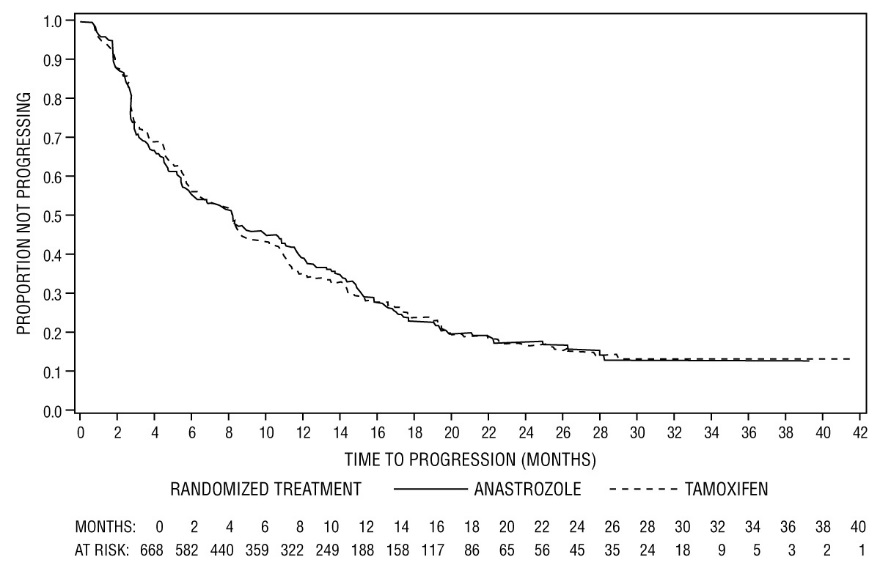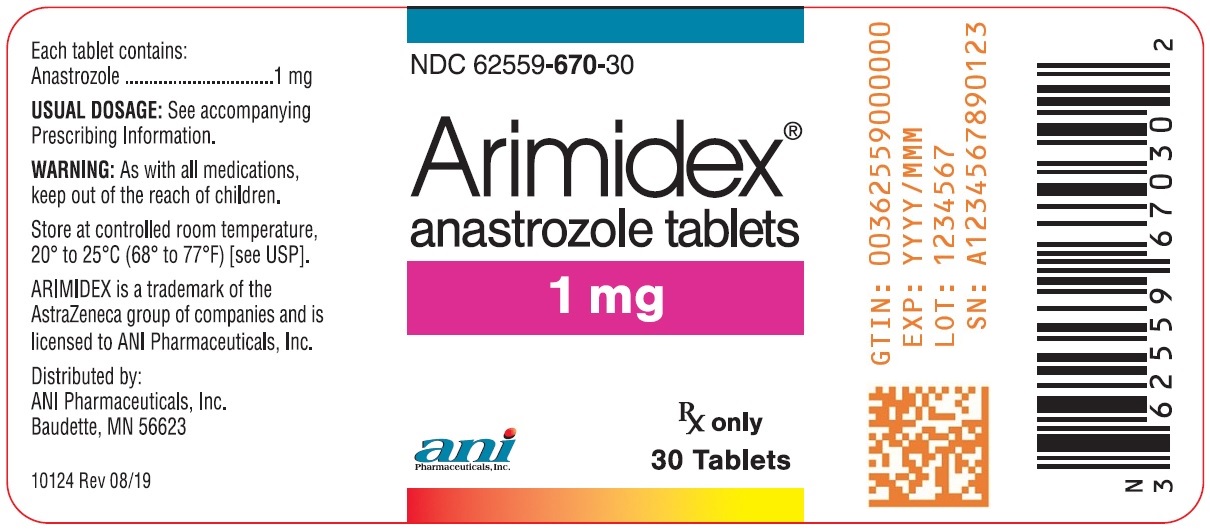 DRUG LABEL: ARIMIDEX
NDC: 62559-670 | Form: TABLET
Manufacturer: ANI Pharmaceuticals, Inc.
Category: prescription | Type: HUMAN PRESCRIPTION DRUG LABEL
Date: 20250708

ACTIVE INGREDIENTS: ANASTROZOLE 1 mg/1 1
INACTIVE INGREDIENTS: LACTOSE MONOHYDRATE; MAGNESIUM STEARATE; HYPROMELLOSE, UNSPECIFIED; POLYETHYLENE GLYCOL 300; POVIDONE, UNSPECIFIED; SODIUM STARCH GLYCOLATE TYPE A POTATO; TITANIUM DIOXIDE

HIGHLIGHTS OF PRESCRIBING INFORMATION

These highlights do not include all the information needed to use ARIMIDEX safely and effectively. See full prescribing information for ARIMIDEX.
ARIMIDEX® (anastrozole) tablet, for oral use
Initial U.S. Approval: 1995

1 INDICATIONS AND USAGE

ARIMIDEX is an aromatase inhibitor indicated for:

- Adjuvant treatment of postmenopausal women with hormone receptor-positive early breast cancer (1.1)
- First-line treatment of postmenopausal women with hormone receptor-positive or hormone receptor-unknown locally advanced or metastatic breast cancer (1.2)
- Treatment of advanced breast cancer in postmenopausal women with disease progression following tamoxifen therapy. Patients with ER-negative disease and patients who did not respond to previous tamoxifen therapy rarely responded to ARIMIDEX (1.3)

2 DOSAGE AND ADMINISTRATION

One 1 mg tablet taken once daily (2.1)

3 DOSAGE FORMS AND STRENGTHS

1 mg tablets (3)

4 CONTRAINDICATIONS

Patients with demonstrated hypersensitivity to ARIMIDEX or any excipient (4)

5 WARNINGS AND PRECAUTIONS

- In women with pre-existing ischemic heart disease, an increased incidence of ischemic cardiovascular events occurred with ARIMIDEX use compared to tamoxifen use. Consider risks and benefits. (5.1, 6.1)
- Decreases in bone mineral density may occur. Consider bone mineral density monitoring. (5.2, 6.1)
- Increases in total cholesterol may occur. Consider cholesterol monitoring. (5.3, 6.1)
- Embryo-Fetal Toxicity: ARIMIDEX may cause fetal harm. Advise patients of the potential risk to a fetus and to use effective contraception. (5.4, 8.1)

6 ADVERSE REACTIONS

In the early breast cancer (ATAC) study, the most common (occurring with an incidence of ≥10%) side effects occurring in women taking ARIMIDEX included: hot flashes, asthenia, arthritis, pain, arthralgia, pharyngitis, hypertension, depression, nausea and vomiting, rash, osteoporosis, fractures, back pain, insomnia, headache, peripheral edema and lymphedema, regardless of causality. (6.1)

In the advanced breast cancer studies, the most common (occurring with an incidence of >10%) side effects occurring in women taking ARIMIDEX included: hot flashes, nausea, asthenia, pain, headache, back pain, bone pain, increased cough, dyspnea, pharyngitis and peripheral edema. (6.1)

To report SUSPECTED ADVERSE REACTIONS, contact ANI Pharmaceuticals, Inc. at 1-800-308-6755 or FDA at 1-800-FDA-1088 or www.fda.gov/medwatch

7 DRUG INTERACTIONS

- Tamoxifen: Do not use in combination with ARIMIDEX. No additional benefit seen over tamoxifen monotherapy. (7.1, 14.1)
- Estrogen-containing products: Combination use may diminish activity of ARIMIDEX. (7.2)

8 USE IN SPECIFIC POPULATIONS

- Lactation: Do not breastfeed. (8.2)
- Females and Males of Reproductive Potential: Verify pregnancy status prior to initiation of ARIMIDEX. (8.3)
- Pediatric patients: Efficacy has not been demonstrated for pubertal boys of adolescent age with gynecomastia or girls with McCune-Albright Syndrome and progressive precocious puberty. (8.4)

FULL PRESCRIBING INFORMATION

1 INDICATIONS AND USAGE

1.1 Adjuvant Treatment

ARIMIDEX is indicated for adjuvant treatment of postmenopausal women with hormone receptor-positive early breast cancer.

1.2 First-Line Treatment

ARIMIDEX is indicated for the first-line treatment of postmenopausal women with hormone receptor-positive or hormone receptor-unknown locally advanced or metastatic breast cancer.

1.3 Second-Line Treatment

ARIMIDEX is indicated for the treatment of advanced breast cancer in postmenopausal women with disease progression following tamoxifen therapy. Patients with ER-negative disease and patients who did not respond to previous tamoxifen therapy rarely responded to ARIMIDEX.

2 DOSAGE AND ADMINISTRATION

2.1 Recommended Dose

The dose of ARIMIDEX is one 1 mg tablet taken once a day. For patients with advanced breast cancer, ARIMIDEX should be continued until tumor progression. ARIMIDEX can be taken with or without food.

For adjuvant treatment of early breast cancer in postmenopausal women, the optimal duration of therapy is unknown. In the ATAC trial, ARIMIDEX was administered for five years [see Clinical Studies (14.1)].

No dosage adjustment is necessary for patients with renal impairment or for elderly patients [see Use in Specific Populations (8.6)].

2.2 Patients with Hepatic Impairment

No changes in dose are recommended for patients with mild-to-moderate hepatic impairment. ARIMIDEX has not been studied in patients with severe hepatic impairment [see Use in Specific Populations (8.7)].

3 DOSAGE FORMS AND STRENGTHS

The tablets are white, biconvex, film-coated containing 1 mg of anastrozole. The tablets are impressed on one side with a logo consisting of a letter “A” (upper case) with an arrowhead attached to the foot of the extended right leg of the “A” and on the reverse with the tablet strength marking “Adx 1”.

4 CONTRAINDICATIONS

Hypersensitivity

ARIMIDEX is contraindicated in any patient who has shown a hypersensitivity reaction to the drug or to any of the excipients. Observed reactions include anaphylaxis, angioedema, and urticaria [see Adverse Reactions (6.2)].

5 WARNINGS AND PRECAUTIONS

5.1 Ischemic Cardiovascular Events

In women with pre-existing ischemic heart disease, an increased incidence of ischemic cardiovascular events was observed with ARIMIDEX in the ATAC trial (17% of patients on ARIMIDEX and 10% of patients on tamoxifen). Consider risk and benefits of ARIMIDEX therapy in patients with pre-existing ischemic heart disease [see Adverse Reactions (6.1)].

5.2 Bone Effects

Results from the ATAC trial bone substudy at 12 and 24 months demonstrated that patients receiving ARIMIDEX had a mean decrease in both lumbar spine and total hip bone mineral density (BMD) compared to baseline. Patients receiving tamoxifen had a mean increase in both lumbar spine and total hip BMD compared to baseline. Consider bone mineral density monitoring in patients treated with ARIMIDEX [see Adverse Reactions (6.1)].

5.3 Cholesterol

During the ATAC trial, more patients receiving ARIMIDEX were reported to have elevated serum cholesterol compared to patients receiving tamoxifen (9% versus 3.5%, respectively) [see Adverse Reactions (6.1)].

5.4 Embryo-Fetal Toxicity

Based on findings from animal studies and its mechanism of action, ARIMIDEX can cause fetal harm when administered to a pregnant woman. Anastrozole caused embryo-fetal toxicities in rats at maternal exposure that were 9 times the human clinical exposure, based on area under the curve (AUC). In rabbits, anastrozole caused pregnancy failure at doses equal to or greater than 16 times the recommended human dose on a mg/m^2 basis. Advise pregnant women and females of reproductive potential of the potential risk to a fetus. Advise females of reproductive potential to use effective contraception during therapy with ARIMIDEX and for at least 3 weeks after the last dose [see Use in Specific Populations (8.1, 8.3) and Clinical Pharmacology (12.1)].

6 ADVERSE REACTIONS

Serious adverse reactions with ARIMIDEX occurring in less than 1 in 10,000 patients, are: 1) skin reactions such as lesions, ulcers, or blisters; 2) allergic reactions with swelling of the face, lips, tongue, and/or throat. This may cause difficulty in swallowing and/or breathing; and 3) changes in blood tests of the liver function, including inflammation of the liver with symptoms that may include a general feeling of not being well, with or without jaundice, liver pain or liver swelling [see Adverse Reactions (6.2)].

Common adverse reactions (occurring with an incidence of ≥10%) in women taking ARIMIDEX included: hot flashes, asthenia, arthritis, pain, arthralgia, hypertension, depression, nausea and vomiting, rash, osteoporosis, fractures, back pain, insomnia, headache, bone pain, peripheral edema, increased cough, dyspnea, pharyngitis and lymphedema.

In the ATAC trial, the most common reported adverse reaction (>0.1%) leading to discontinuation of therapy for both treatment groups was hot flashes, although there were fewer patients who discontinued therapy as a result of hot flashes in the ARIMIDEX group.

Because clinical trials are conducted under widely varying conditions, adverse reaction rates observed in the clinical trials of a drug cannot be directly compared to rates in the clinical trials of another drug and may not reflect the rates observed in practice.

6.1 Clinical Trials Experience

Adjuvant Therapy

Adverse reaction data for adjuvant therapy are based on the ATAC trial [see Clinical Studies (14.1)]. The median duration of adjuvant treatment for safety evaluation was 59.8 months and 59.6 months for patients receiving ARIMIDEX 1 mg and tamoxifen 20 mg, respectively.

Adverse reactions occurring with an incidence of at least 5% in either treatment group during treatment or within 14 days of the end of treatment are presented in Table 1.

Table 1 - Adverse reactions occurring with an incidence of at least 5% in either treatment group during treatment, or within 14 days of the end of treatment in the ATAC trial [The combination arm was discontinued due to lack of efficacy benefit at 33 months of follow-up.]
Body system and adverse reactions by COSTART preferred term [COSTART Coding Symbols for Thesaurus of Adverse Reaction Terms.] [A patient may have had more than 1 adverse reaction, including more than 1 adverse reaction in the same body system.] | ARIMIDEX 1 mg (N [N=Number of patients receiving the treatment.] = 3092) | Tamoxifen 20 mg (N = 3094)
Body as a whole
Asthenia | 575 (19) | 544 (18)
Pain | 533 (17) | 485 (16)
Back pain | 321 (10) | 309 (10)
Headache | 314 (10) | 249 (8)
Abdominal pain | 271 (9) | 276 (9)
Infection | 285 (9) | 276 (9)
Accidental injury | 311 (10) | 303 (10)
Flu syndrome | 175 (6) | 195 (6)
Chest pain | 200 (7) | 150 (5)
Neoplasm | 162 (5) | 144 (5)
Cyst | 138 (5) | 162 (5)
Cardiovascular
Vasodilatation | 1104 (36) | 1264 (41)
Hypertension | 402 (13) | 349 (11)
Digestive
Nausea | 343 (11) | 335 (11)
Constipation | 249 (8) | 252 (8)
Diarrhea | 265 (9) | 216 (7)
Dyspepsia | 206 (7) | 169 (6)
Gastrointestinal disorder | 210 (7) | 158 (5)
Hemic and lymphatic
Lymphedema | 304 (10) | 341 (11)
Anemia | 113 (4) | 159 (5)
Metabolic and nutritional
Peripheral edema | 311 (10) | 343 (11)
Weight gain | 285 (9) | 274 (9)
Hypercholesterolemia | 278 (9) | 108 (3.5)
Musculoskeletal
Arthritis | 512 (17) | 445 (14)
Arthralgia | 467 (15) | 344 (11)
Osteoporosis | 325 (11) | 226 (7)
Fracture | 315 (10) | 209 (7)
Bone pain | 201 (7) | 185 (6)
Arthrosis | 207 (7) | 156 (5)
Joint Disorder | 184 (6) | 160 (5)
Myalgia | 179 (6) | 160 (5)
Nervous system
Depression | 413 (13) | 382 (12)
Insomnia | 309 (10) | 281 (9)
Dizziness | 236 (8) | 234 (8)
Anxiety | 195 (6) | 180 (6)
Paresthesia | 215 (7) | 145 (5)
Respiratory
Pharyngitis | 443 (14) | 422 (14)
Cough increased | 261 (8) | 287 (9)
Dyspnea | 234 (8) | 237 (8)
Sinusitis | 184 (6) | 159 (5)
Bronchitis | 167 (5) | 153 (5)
Skin and appendages
Rash | 333 (11) | 387 (13)
Sweating | 145 (5) | 177 (6)
Special Senses
Cataract Specified | 182 (6) | 213 (7)
Urogenital
Leukorrhea | 86 (3) | 286 (9)
Urinary tract infection | 244 (8) | 313 (10)
Breast pain | 251 (8) | 169 (6)
Breast Neoplasm | 164 (5) | 139 (5)
Vulvovaginitis | 194 (6) | 150 (5)
Vaginal Hemorrhage [Vaginal Hemorrhage without further diagnosis.] | 122 (4) | 180 (6)
Vaginitis | 125 (4) | 158 (5)

Certain adverse reactions and combinations of adverse reactions were prospectively specified for analysis, based on the known pharmacologic properties and side effect profiles of the two drugs (see Table 2).

Table 2 - Number of Patients with Pre-specified Adverse Reactions in ATAC Trial [Patients with multiple events in the same category are counted only once in that category.]
 | ARIMIDEX N=3092 (%) | Tamoxifen N=3094 (%) | Odds-ratio | 95% CI
Hot Flashes | 1104 (36) | 1264 (41) | 0.80 | 0.73 − 0.89
Musculoskeletal Events [Refers to joint symptoms, including joint disorder, arthritis, arthrosis and arthralgia.] | 1100 (36) | 911 (29) | 1.32 | 1.19 − 1.47
Fatigue/Asthenia | 575 (19) | 544 (18) | 1.07 | 0.94 − 1.22
Mood Disturbances | 597 (19) | 554 (18) | 1.10 | 0.97 − 1.25
Nausea and Vomiting | 393 (13) | 384 (12) | 1.03 | 0.88 − 1.19
All Fractures | 315 (10) | 209 (7) | 1.57 | 1.30 − 1.88
Fractures of Spine, Hip, or Wrist | 133 (4) | 91 (3) | 1.48 | 1.13 − 1.95
Wrist/Colles’ fractures | 67 (2) | 50 (2)
Spine fractures | 43 (1) | 22 (1)
Hip fractures | 28 (1) | 26 (1)
Cataracts | 182 (6) | 213 (7) | 0.85 | 0.69 − 1.04
Vaginal Bleeding | 167 (5) | 317 (10) | 0.50 | 0.41 − 0.61
Ischemic Cardiovascular Disease | 127 (4) | 104 (3) | 1.23 | 0.95 − 1.60
Vaginal Discharge | 109 (4) | 408 (13) | 0.24 | 0.19 − 0.30
Venous Thromboembolic Events | 87 (3) | 140 (5) | 0.61 | 0.47 − 0.80
Deep Venous Thromboembolic Events | 48 (2) | 74 (2) | 0.64 | 0.45 − 0.93
Ischemic Cerebrovascular Event | 62 (2) | 88 (3) | 0.70 | 0.50 − 0.97
Endometrial Cancer [Percentages calculated based upon the numbers of patients with an intact uterus at baseline.] | 4 (0.2) | 13 (0.6) | 0.31 | 0.10 − 0.94

Ischemic Cardiovascular Events

Between treatment arms in the overall population of 6186 patients, there was no statistical difference in ischemic cardiovascular events (4% ARIMIDEX vs. 3% tamoxifen). In the overall population, angina pectoris was reported in 71/3092 (2.3%) patients in the ARIMIDEX arm and 51/3094 (1.6%) patients in the tamoxifen arm; myocardial infarction was reported in 37/3092 (1.2%) patients in the ARIMIDEX arm and 34/3094 (1.1%) patients in the tamoxifen arm.

In women with pre-existing ischemic heart disease 465/6186 (7.5%), the incidence of ischemic cardiovascular events was 17% in patients on ARIMIDEX and 10% in patients on tamoxifen. In this patient population, angina pectoris was reported in 25/216 (11.6%) patients receiving ARIMIDEX and 13/249 (5.2%) patients receiving tamoxifen; myocardial infarction was reported in 2/216 (0.9%) patients receiving ARIMIDEX and 8/249 (3.2%) patients receiving tamoxifen.

Bone Mineral Density Findings

Results from the ATAC trial bone substudy at 12 and 24 months demonstrated that patients receiving ARIMIDEX had a mean decrease in both lumbar spine and total hip bone mineral density (BMD) compared to baseline. Patients receiving tamoxifen had a mean increase in both lumbar spine and total hip BMD compared to baseline.

Because ARIMIDEX lowers circulating estrogen levels it may cause a reduction in bone mineral density.

A post-marketing trial assessed the combined effects of ARIMIDEX and the bisphosphonate risedronate on changes from baseline in BMD and markers of bone resorption and formation in postmenopausal women with hormone receptor-positive early breast cancer. All patients received calcium and vitamin D supplementation. At 12 months, small reductions in lumbar spine bone mineral density were noted in patients not receiving bisphosphonates. Bisphosphonate treatment preserved bone density in most patients at risk of fracture.

Postmenopausal women with early breast cancer scheduled to be treated with ARIMIDEX should have their bone status managed according to treatment guidelines already available for postmenopausal women at similar risk of fragility fracture.

Cholesterol

During the ATAC trial, more patients receiving ARIMIDEX were reported to have an elevated serum cholesterol compared to patients receiving tamoxifen (9% versus 3.5%, respectively).

A post-marketing trial also evaluated any potential effects of ARIMIDEX on lipid profile. In the primary analysis population for lipids (ARIMIDEX alone), there was no clinically significant change in LDL-C from baseline to 12 months and HDL-C from baseline to 12 months.

In secondary population for lipids (ARIMIDEX+risedronate), there also was no clinically significant change in LDL-C and HDL-C from baseline to 12 months.

In both populations for lipids, there was no clinically significant difference in total cholesterol (TC) or serum triglycerides (TG) at 12 months compared with baseline.

In this trial, treatment for 12 months with ARIMIDEX alone had a neutral effect on lipid profile. Combination treatment with ARIMIDEX and risedronate also had a neutral effect on lipid profile.

The trial provides evidence that postmenopausal women with early breast cancer scheduled to be treated with ARIMIDEX should be managed using the current National Cholesterol Education Program guidelines for cardiovascular risk-based management of individual patients with LDL elevations.

Other Adverse Reactions

Patients receiving ARIMIDEX had an increase in joint disorders (including arthritis, arthrosis and arthralgia) compared with patients receiving tamoxifen. Patients receiving ARIMIDEX had an increase in the incidence of all fractures (specifically fractures of spine, hip and wrist) [315 (10%)] compared with patients receiving tamoxifen [209 (7%)].

Patients receiving ARIMIDEX had a higher incidence of carpal tunnel syndrome [78 (2.5%)] compared with patients receiving tamoxifen [22 (0.7%)].

Vaginal bleeding occurred more frequently in the tamoxifen-treated patients versus the ARIMIDEX-treated patients 317 (10%) versus 167 (5%), respectively.

Patients receiving ARIMIDEX had a lower incidence of hot flashes, vaginal bleeding, vaginal discharge, endometrial cancer, venous thromboembolic events and ischemic cerebrovascular events compared with patients receiving tamoxifen.

10-year median follow-up Safety Results from the ATAC Trial

Results are consistent with the previous analyses.

Serious adverse reactions were similar between ARIMIDEX (50%) and tamoxifen (51%).

- Cardiovascular events were consistent with the known safety profiles of ARIMIDEX and tamoxifen.
- The cumulative incidences of all first fractures (both serious and non-serious, occurring either during or after treatment) was higher in the ARIMIDEX group (15%) compared to the tamoxifen group (11%). This increased first fracture rate during treatment did not continue in the post-treatment follow-up period.
- The cumulative incidence of new primary cancers was similar in the ARIMIDEX group (13.7%) compared to the tamoxifen group (13.9%). Consistent with the previous analyses, endometrial cancer was higher in the tamoxifen group (0.8%) compared to the ARIMIDEX group (0.2%).
- The overall number of deaths (during or off-trial treatment) was similar between the treatment groups. There were more deaths related to breast cancer in the tamoxifen than in the ARIMIDEX treatment group.

First-Line Therapy

Adverse reactions occurring with an incidence of at least 5% in either treatment group of trials 0030 and 0027 during or within 2 weeks of the end of treatment are shown in Table 3.

Table 3 - Adverse Reactions Occurring with an Incidence of at Least 5% in Trials 0030 and 0027
Body system Adverse Reaction [A patient may have had more than 1 adverse event.] | Number (%) of subjects
Body system Adverse Reaction [A patient may have had more than 1 adverse event.] | ARIMIDEX (N=506) | Tamoxifen (N=511)
Whole body
Asthenia | 83 (16) | 81 (16)
Pain | 70 (14) | 73 (14)
Back pain | 60 (12) | 68 (13)
Headache | 47 (9) | 40 (8)
Abdominal pain | 40 (8) | 38 (7)
Chest pain | 37 (7) | 37 (7)
Flu syndrome | 35 (7) | 30 (6)
Pelvic pain | 23 (5) | 30 (6)
Cardiovascular
Vasodilation | 128 (25) | 106 (21)
Hypertension | 25 (5) | 36 (7)
Digestive
Nausea | 94 (19) | 106 (21)
Constipation | 47 (9) | 66 (13)
Diarrhea | 40 (8) | 33 (6)
Vomiting | 38 (8) | 36 (7)
Anorexia | 26 (5) | 46 (9)
Metabolic and Nutritional
Peripheral edema | 51 (10) | 41 (8)
Musculoskeletal
Bone pain | 54 (11) | 52 (10)
Nervous
Dizziness | 30 (6) | 22 (4)
Insomnia | 30 (6) | 38 (7)
Depression | 23 (5) | 32 (6)
Hypertonia | 16 (3) | 26 (5)
Respiratory
Cough increased | 55 (11) | 52 (10)
Dyspnea | 51 (10) | 47 (9)
Pharyngitis | 49 (10) | 68 (13)
Skin and appendages
Rash | 38 (8) | 34 (8)
Urogenital
Leukorrhea | 9 (2) | 31 (6)

Less frequent adverse experiences reported in patients receiving ARIMIDEX 1 mg in either Trial 0030 or Trial 0027 were similar to those reported for second-line therapy.

Based on results from second-line therapy and the established safety profile of tamoxifen, the incidences of 9 pre-specified adverse event categories potentially causally related to one or both of the therapies because of their pharmacology were statistically analyzed. No significant differences were seen between treatment groups.

Table 4 - Number of Patients with Pre-specified Adverse Reactions in Trials 0030 and 0027
Adverse Reaction [A patient may have had more than 1 adverse reaction.] | Number (n) and Percentage of Patients
Adverse Reaction [A patient may have had more than 1 adverse reaction.] | ARIMIDEX 1 mg (N=506) n (%) | NOLVADEX 20 mg (N=511) n (%)
Depression | 23 (5) | 32 (6)
Tumor Flare | 15 (3) | 18 (4)
Thromboembolic Disease [Includes pulmonary embolus, thrombophlebitis, retinal vein thrombosis.] | 18 (4) | 33 (6)
Venous | 5 | 15
Coronary and Cerebral [Includes myocardial infarction, myocardial ischemia, angina pectoris, cerebrovascular accident, cerebral ischemia and cerebral infarct.] | 13 | 19
Gastrointestinal Disturbance | 170 (34) | 196 (38)
Hot Flushes | 134 (26) | 118 (23)
Vaginal Dryness | 9 (2) | 3 (1)
Lethargy | 6 (1) | 15 (3)
Vaginal Bleeding | 5 (1) | 11 (2)
Weight Gain | 11 (2) | 8 (2)

Second-Line Therapy

ARIMIDEX was tolerated in two controlled clinical trials (i.e., Trials 0004 and 0005), with less than 3.3% of the ARIMIDEX-treated patients and 4.0% of the megestrol acetate-treated patients withdrawing due to an adverse reaction.

The principal adverse reaction more common with ARIMIDEX than megestrol acetate was diarrhea. Adverse reactions reported in greater than 5% of the patients in any of the treatment groups in these two controlled clinical trials, regardless of causality, are presented below:

Table 5 - Number (n) and Percentage of Patients with Adverse Reactions in Trials 0004 and 0005
Adverse Reaction [A patient may have had more than one adverse reaction.] | ARIMIDEX |  | ARIMIDEX |  | Megestrol Acetate
Adverse Reaction [A patient may have had more than one adverse reaction.] | 1 mg |  | 10 mg |  | 160 mg
Adverse Reaction [A patient may have had more than one adverse reaction.] | (N=262) |  | (N=246) |  | (N=253)
Adverse Reaction [A patient may have had more than one adverse reaction.] | n | % | n | % | n | %
Asthenia | 42 | (16) | 33 | (13) | 47 | (19)
Nausea | 41 | (16) | 48 | (20) | 28 | (11)
Headache | 34 | (13) | 44 | (18) | 24 | (9)
Hot Flashes | 32 | (12) | 29 | (11) | 21 | (8)
Pain | 28 | (11) | 38 | (15) | 29 | (11)
Back Pain | 28 | (11) | 26 | (11) | 19 | (8)
Dyspnea | 24 | (9) | 27 | (11) | 53 | (21)
Vomiting | 24 | (9) | 26 | (11) | 16 | (6)
Cough Increased | 22 | (8) | 18 | (7) | 19 | (8)
Diarrhea | 22 | (8) | 18 | (7) | 7 | (3)
Constipation | 18 | (7) | 18 | (7) | 21 | (8)
Abdominal Pain | 18 | (7) | 14 | (6) | 18 | (7)
Anorexia | 18 | (7) | 19 | (8) | 11 | (4)
Bone Pain | 17 | (6) | 26 | (12) | 19 | (8)
Pharyngitis | 16 | (6) | 23 | (9) | 15 | (6)
Dizziness | 16 | (6) | 12 | (5) | 15 | (6)
Rash | 15 | (6) | 15 | (6) | 19 | (8)
Dry Mouth | 15 | (6) | 11 | (4) | 13 | (5)
Peripheral Edema | 14 | (5) | 21 | (9) | 28 | (11)
Pelvic Pain | 14 | (5) | 17 | (7) | 13 | (5)
Depression | 14 | (5) | 6 | (2) | 5 | (2)
Chest Pain | 13 | (5) | 18 | (7) | 13 | (5)
Paresthesia | 12 | (5) | 15 | (6) | 9 | (4)
Vaginal Hemorrhage | 6 | (2) | 4 | (2) | 13 | (5)
Weight Gain | 4 | (2) | 9 | (4) | 30 | (12)
Sweating | 4 | (2) | 3 | (1) | 16 | (6)
Increased Appetite | 0 | (0) | 1 | (0) | 13 | (5)

Other less frequent (2% to 5%) adverse reactions reported in patients receiving ARIMIDEX 1 mg in either Trial 0004 or Trial 0005 are listed below. These adverse experiences are listed by body system and are in order of decreasing frequency within each body system regardless of assessed causality.

Body as a Whole: Flu syndrome; fever; neck pain; malaise; accidental injury; infection

Cardiovascular: Hypertension; thrombophlebitis

Hepatic: Gamma GT increased; SGOT increased; SGPT increased

Hematologic: Anemia; leukopenia

Metabolic and Nutritional: Alkaline phosphatase increased; weight loss

Mean serum total cholesterol levels increased by 0.5 mmol/L among patients receiving ARIMIDEX. Increases in LDL cholesterol have been shown to contribute to these changes.

Musculoskeletal: Myalgia; arthralgia; pathological fracture

Nervous: Somnolence; confusion; insomnia; anxiety; nervousness

Respiratory: Sinusitis; bronchitis; rhinitis

Skin and Appendages: Hair thinning (alopecia); pruritus

Urogenital: Urinary tract infection; breast pain

The incidences of the following adverse reaction groups potentially causally related to one or both of the therapies because of their pharmacology, were statistically analyzed: weight gain, edema, thromboembolic disease, gastrointestinal disturbance, hot flushes, and vaginal dryness. These six groups, and the adverse reactions captured in the groups, were prospectively defined. The results are shown in the table below.

Table 6 - Number (n) and Percentage of Patients with Pre-specified Adverse Reactions in Trials 0004 and 0005
Adverse Reaction Group | ARIMIDEX |  | ARIMIDEX |  | Megestrol Acetate
Adverse Reaction Group | 1 mg |  | 10 mg |  | 160 mg
Adverse Reaction Group | (N=262) |  | (N=246) |  | (N=253)
Adverse Reaction Group | n | (%) | n | (%) | n | (%)
Gastrointestinal Disturbance | 77 | (29) | 81 | (33) | 54 | (21)
Hot Flushes | 33 | (13) | 29 | (12) | 35 | (14)
Edema | 19 | (7) | 28 | (11) | 35 | (14)
Thromboembolic Disease | 9 | (3) | 4 | (2) | 12 | (5)
Vaginal Dryness | 5 | (2) | 3 | (1) | 2 | (1)
Weight Gain | 4 | (2) | 10 | (4) | 30 | (12)

6.2 Post-Marketing Experience

These adverse reactions are reported voluntarily from a population of uncertain size. Therefore, it is not always possible to estimate reliably their frequency or establish a causal relationship to drug exposure. The following have been reported in post-approval use of ARIMIDEX:

- Hepatobiliary events including increases in alkaline phosphatase, alanine aminotransferase, aspartate aminotransferase, gamma-GT, and bilirubin; hepatitis
- Rash including cases of mucocutaneous disorders such as erythema multiforme and Stevens-Johnson syndrome
- Cases of allergic reactions including angioedema, urticaria and anaphylaxis [see Contraindications (4)]
- Myalgia and hypercalcemia (with or without an increase in parathyroid hormone)
- Tendon disorders including tendon rupture, tendonitis, tenosynovitis, and tenosynovitis stenosans (trigger finger)

7 DRUG INTERACTIONS

7.1 Tamoxifen

Co-administration of anastrozole and tamoxifen in breast cancer patients reduced anastrozole plasma concentration by 27%. However, the co-administration of anastrozole and tamoxifen did not affect the pharmacokinetics of tamoxifen or N-desmethyltamoxifen. At a median follow-up of 33 months, the combination of ARIMIDEX and tamoxifen did not demonstrate any efficacy benefit when compared with tamoxifen in all patients as well as in the hormone receptor-positive subpopulation. This treatment arm was discontinued from the trial [see Clinical Studies (14.1)]. Based on clinical and pharmacokinetic results from the ATAC trial, tamoxifen should not be administered with anastrozole.

7.2 Estrogen

Estrogen-containing therapies should not be used with ARIMIDEX as they may diminish its pharmacological action.

7.3 Warfarin

In a study conducted in 16 male volunteers, anastrozole did not alter the exposure (as measured by Cmax and AUC) and anticoagulant activity (as measured by prothrombin time, activated partial thromboplastin time, and thrombin time) of both R- and S-warfarin.

7.4 Cytochrome P450

Based on in vitro and in vivo results, it is unlikely that co-administration of ARIMIDEX 1 mg will affect other drugs as a result of inhibition of cytochrome P450 [see Clinical Pharmacology (12.3)].

8 USE IN SPECIFIC POPULATIONS

8.1 Pregnancy

Risk Summary

Based on findings from animal studies and its mechanism of action, ARIMIDEX may cause fetal harm when administered to a pregnant woman [see Clinical Pharmacology (12.1)]. There are no studies of ARIMIDEX use in pregnant women. Anastrozole caused embryo-fetal toxicities in rats at maternal exposure that were 9 times the human clinical exposure, based on area under the curve (AUC). In rabbits, anastrozole caused pregnancy failure at doses equal to or greater than 16 times the recommended human dose on a mg/m^2 basis. Advise pregnant women and females of reproductive potential of the potential risk to a fetus.

The background risk of major birth defects and miscarriage for the indicated population is unknown. In the U.S. general population, the estimated background risk of major birth defects and miscarriage in clinically recognized pregnancies is 2% to 4% and 15% to 20%, respectively.

Data

Animal Data

In animal reproduction studies, pregnant rats and rabbits received anastrozole during organogenesis at doses equal to or greater than 0.1 and 0.02 mg/kg/day, respectively, (about 1 and 1/3 the recommended human dose on a mg/m^2 basis, respectively). In both species, anastrozole crossed the placenta, and there was increased pregnancy loss (increased pre- and/or post-implantation loss, increased resorption, and decreased numbers of live fetuses). In rats, these effects were dose related, and placental weights were significantly increased at doses equal to or greater than 0.1 mg/kg/day. Fetotoxicity, including delayed fetal development (i.e., incomplete ossification and depressed fetal body weights), occurred in rats at anastrozole doses of 1 mg/kg/day that produced peak plasma levels 19 times higher than serum levels in humans at the therapeutic dose (AUC0-24hr 9 times higher). In rabbits, anastrozole caused pregnancy failure at doses equal to or greater than 1.0 mg/kg/day (about 16 times the recommended human dose on a mg/m^2 basis).

8.2 Lactation

Risk Summary

There are no data on the presence of anastrozole or its metabolites in human milk, or its effects on the breast-fed child or on milk production. Because many drugs are excreted in human milk and because of the tumorigenicity shown for anastrozole in animal studies, or the potential for serious adverse reactions in the breast-fed child from ARIMIDEX, advise lactating women not to breastfeed during treatment with ARIMIDEX and for 2 weeks after the last dose.

8.3 Females and Males of Reproductive Potential

Pregnancy Testing

Verify the pregnancy status of females of reproductive potential prior to initiation of ARIMIDEX.

Contraception

Females

Based on animal studies, ARIMIDEX can cause fetal harm when administered to a pregnant woman [see Use in Specific Populations (8.1)]. Advise females of reproductive potential to use effective contraception during treatment with ARIMIDEX and for at least 3 weeks after the last dose.

Infertility

Females

Based on studies in female animals, ARIMIDEX may impair fertility in females of reproductive potential [see Nonclinical Toxicology (13.1)].

8.4 Pediatric Use

Clinical studies in pediatric patients included a placebo-controlled trial in pubertal boys of adolescent age with gynecomastia and a single-arm trial in girls with McCune-Albright Syndrome and progressive precocious puberty. The efficacy of ARIMIDEX in the treatment of pubertal gynecomastia in adolescent boys and in the treatment of precocious puberty in girls with McCune-Albright Syndrome has not been demonstrated.

Gynecomastia Study

A randomized, double-blind, placebo-controlled, multi-center study enrolled 80 boys with pubertal gynecomastia aged 11 to 18 years. Patients were randomized to a daily regimen of either ARIMIDEX 1 mg or placebo. After 6 months of treatment there was no statistically significant difference in the percentage of patients who experienced a ≥50% reduction in gynecomastia (primary efficacy analysis). Secondary efficacy analyses (absolute change in breast volume, the percentage of patients who had any reduction in the calculated volume of gynecomastia, breast pain resolution) were consistent with the primary efficacy analysis. Serum estradiol concentrations at Month 6 of treatment were reduced by 15.4% in the ARIMIDEX group and 4.5% in the placebo group.

Adverse reactions that were assessed as treatment-related by the investigators occurred in 16.3% of the ARIMIDEX-treated patients and 8.1% of the placebo-treated patients with the most frequent being acne (7% ARIMIDEX and 2.7% placebo) and headache (7% ARIMIDEX and 0% placebo); all other adverse reactions showed small differences between treatment groups. One patient treated with ARIMIDEX discontinued the trial because of testicular enlargement. The mean baseline-subtracted change in testicular volume after 6 months of treatment was + 6.6 ± 7.9 cm^3 in the ARIMIDEX-treated patients and + 5.2 ± 8.0 cm^3 in the placebo group.

McCune-Albright Syndrome Study

A multi-center, single-arm, open-label study was conducted in 28 girls with McCune-Albright Syndrome and progressive precocious puberty aged 2 to <10 years. All patients received a 1 mg daily dose of ARIMIDEX. The trial duration was 12 months. Patients were enrolled on the basis of a diagnosis of typical (27/28) or atypical (1/27) McCune-Albright Syndrome, precocious puberty, history of vaginal bleeding, and/or advanced bone age. Patients’ baseline characteristics included the following: a mean chronological age of 5.9 ± 2.0 years, a mean bone age of 8.6 ± 2.6 years, a mean growth rate of 7.9 ± 2.9 cm/year and a mean Tanner stage for breast of 2.7 ± 0.81. Compared to pre-treatment data there were no on-treatment statistically significant reductions in the frequency of vaginal bleeding days, or in the rate of increase of bone age (defined as a ratio between the change in bone age over the change of chronological age). There were no clinically significant changes in Tanner staging, mean ovarian volume, mean uterine volume and mean predicted adult height. A small but statistically significant reduction of growth rate from 7.9 ± 2.9 cm/year to 6.5 ± 2.8 cm/year was observed but the absence of a control group precludes attribution of this effect to treatment or to other confounding factors such as variations in endogenous estrogen levels commonly seen in McCune-Albright Syndrome patients.

Five patients (18%) experienced adverse reactions that were considered possibly related to ARIMIDEX. These were nausea, acne, pain in an extremity, increased alanine transaminase and aspartate transaminase, and allergic dermatitis.

Pharmacokinetics in Pediatric Patients

Following 1 mg once daily multiple administration in pediatric patients, the mean time to reach the maximum anastrozole concentration was 1 hr. The mean (range) disposition parameters of anastrozole in pediatric patients were described by a CL/F of 1.54 L/h (0.77-4.53 L/h) and V/F of 98.4 L (50.7-330.0 L). The terminal elimination half-life was 46.8 h, which was similar to that observed in postmenopausal women treated with anastrozole for breast cancer. Based on a population pharmacokinetic analysis, the pharmacokinetics of anastrozole was similar in boys with pubertal gynecomastia and girls with McCune-Albright Syndrome.

8.5 Geriatric Use

In studies 0030 and 0027, about 50% of patients were 65 or older. Patients ≥ 65 years of age had moderately better tumor response and time to tumor progression than patients < 65 years of age regardless of randomized treatment. In studies 0004 and 0005, 50% of patients were 65 or older. Response rates and time to progression were similar for the over 65 and younger patients.

In the ATAC study, 45% of patients were 65 years of age or older. The efficacy of ARIMIDEX compared to tamoxifen in patients who were 65 years or older (N=1413 for ARIMIDEX and N=1410 for tamoxifen, the hazard ratio for disease-free survival was 0.93 [95% CI: 0.80, 1.08]) was less than efficacy observed in patients who were less than 65 years of age (N=1712 for ARIMIDEX and N=1706 for tamoxifen, the hazard ratio for disease-free survival was 0.79 [95% CI: 0.67, 0.94]).

The pharmacokinetics of anastrozole are not affected by age.

8.6 Renal Impairment

Since only about 10% of anastrozole is excreted unchanged in the urine, the renal impairment does not influence the total body clearance. Dosage adjustment in patients with renal impairment is not necessary [see Dosage and Administration (2.1) and Clinical Pharmacology (12.3)].

8.7 Hepatic Impairment

The plasma anastrozole concentrations in the subjects with hepatic cirrhosis were within the range of concentrations seen in normal subjects across all clinical trials. Therefore, dosage adjustment is also not necessary in patients with stable hepatic cirrhosis. ARIMIDEX has not been studied in patients with severe hepatic impairment [see Dosage and Administration (2.2) and Clinical Pharmacology (12.3)].

10 OVERDOSAGE

Clinical trials have been conducted with ARIMIDEX, up to 60 mg in a single dose given to healthy male volunteers and up to 10 mg daily given to postmenopausal women with advanced breast cancer; these dosages were tolerated. A single dose of ARIMIDEX that results in life-threatening symptoms has not been established. There is no specific antidote to overdosage and treatment must be symptomatic. In the management of an overdose, consider that multiple agents may have been taken. Vomiting may be induced if the patient is alert. Dialysis may be helpful because ARIMIDEX is not highly protein bound. General supportive care, including frequent monitoring of vital signs and close observation of the patient, is indicated.

11 DESCRIPTION

ARIMIDEX (anastrozole) tablets for oral administration contain 1 mg of anastrozole, a non-steroidal aromatase inhibitor. It is chemically described as 1,3-Benzenediacetonitrile, a, a, a', a'-tetramethyl-5-(1H-1,2,4-triazol-1-ylmethyl). Its molecular formula is C17H19N5 and its structural formula is:

Anastrozole is an off-white powder with a molecular weight of 293.4. Anastrozole has moderate aqueous solubility (0.5 mg/mL at 25°C); solubility is independent of pH in the physiological range. Anastrozole is freely soluble in methanol, acetone, ethanol, and tetrahydrofuran, and very soluble in acetonitrile.

Each tablet contains as inactive ingredients: lactose, magnesium stearate, hypromellose, polyethylene glycol, povidone, sodium starch glycolate, and titanium dioxide.

12 CLINICAL PHARMACOLOGY

12.1 Mechanism of Action

The growth of many cancers of the breast is stimulated or maintained by estrogens.

In postmenopausal women, estrogens are mainly derived from the action of the aromatase enzyme, which converts adrenal androgens (primarily androstenedione and testosterone) to estrone and estradiol. The suppression of estrogen biosynthesis in peripheral tissues and in the cancer tissue itself can therefore be achieved by specifically inhibiting the aromatase enzyme.

Anastrozole is a selective non-steroidal aromatase inhibitor. It significantly lowers serum estradiol concentrations and has no detectable effect on formation of adrenal corticosteroids or aldosterone.

12.2 Pharmacodynamics

Effect on Estradiol

Mean serum concentrations of estradiol were evaluated in multiple daily dosing trials with 0.5, 1, 3, 5, and 10 mg of ARIMIDEX in postmenopausal women with advanced breast cancer. Clinically significant suppression of serum estradiol was seen with all doses. Doses of 1 mg and higher resulted in suppression of mean serum concentrations of estradiol to the lower limit of detection (3.7 pmol/L). The recommended daily dose, ARIMIDEX 1 mg, reduced estradiol by approximately 70% within 24 hours and by approximately 80% after 14 days of daily dosing. Suppression of serum estradiol was maintained for up to 6 days after cessation of daily dosing with ARIMIDEX 1 mg.

The effect of ARIMIDEX in premenopausal women with early or advanced breast cancer has not been studied. Because aromatization of adrenal androgens is not a significant source of estradiol in premenopausal women, ARIMIDEX would not be expected to lower estradiol levels in premenopausal women.

Effect on Corticosteroids

In multiple daily dosing trials with 3, 5, and 10 mg, the selectivity of anastrozole was assessed by examining effects on corticosteroid synthesis. For all doses, anastrozole did not affect cortisol or aldosterone secretion at baseline or in response to ACTH. No glucocorticoid or mineralocorticoid replacement therapy is necessary with anastrozole.

Other Endocrine Effects

In multiple daily dosing trials with 5 and 10 mg, thyroid stimulating hormone (TSH) was measured; there was no increase in TSH during the administration of ARIMIDEX. ARIMIDEX does not possess direct progestogenic, androgenic, or estrogenic activity in animals, but does perturb the circulating levels of progesterone, androgens, and estrogens.

12.3 Pharmacokinetics

Absorption

Inhibition of aromatase activity is primarily due to anastrozole, the parent drug. Absorption of anastrozole is rapid and maximum plasma concentrations typically occur within 2 hours of dosing under fasted conditions. Studies with radiolabeled drug have demonstrated that orally administered anastrozole is well absorbed into the systemic circulation. Food reduces the rate but not the overall extent of anastrozole absorption. The mean Cmax of anastrozole decreased by 16% and the median Tmax was delayed from 2 to 5 hours when anastrozole was administered 30 minutes after food. The pharmacokinetics of anastrozole are linear over the dose range of 1 to 20 mg, and do not change with repeated dosing. The pharmacokinetics of anastrozole were similar in patients and healthy volunteers.

Distribution

Steady-state plasma levels are approximately 3- to 4-fold higher than levels observed after a single dose of ARIMIDEX. Plasma concentrations approach steady-state levels at about 7 days of once daily dosing. Anastrozole is 40% bound to plasma proteins in the therapeutic range.

Metabolism

Metabolism of anastrozole occurs by N-dealkylation, hydroxylation and glucuronidation. Three metabolites of anastrozole (triazole, a glucuronide conjugate of hydroxy-anastrozole, and a glucuronide conjugate of anastrozole itself) have been identified in human plasma and urine. The major circulating metabolite of anastrozole, triazole, lacks pharmacologic activity.

Anastrozole inhibited reactions catalyzed by cytochrome P450 1A2, 2C8/9, and 3A4 in vitro with Ki values which were approximately 30 times higher than the mean steady-state Cmax values observed following a 1 mg daily dose. Anastrozole had no inhibitory effect on reactions catalyzed by cytochrome P450 2A6 or 2D6 in vitro. Administration of a single 30 mg/kg or multiple 10 mg/kg doses of anastrozole to healthy subjects had no effect on the clearance of antipyrine or urinary recovery of antipyrine metabolites.

Excretion

Eighty-five percent of radiolabeled anastrozole was recovered in feces and urine. Hepatic metabolism accounts for approximately 85% of anastrozole elimination. Renal elimination accounts for approximately 10% of total clearance. The mean elimination half-life of anastrozole is 50 hours.

Effect of Gender and Age

Anastrozole pharmacokinetics have been investigated in postmenopausal female volunteers and patients with breast cancer. No age-related effects were seen over the range <50 to >80 years.

Effect of Race

Estradiol and estrone sulfate serum levels were similar between Japanese and Caucasian postmenopausal women who received 1 mg of anastrozole daily for 16 days. Anastrozole mean steady-state minimum plasma concentrations in Caucasian and Japanese postmenopausal women were 25.7 and 30.4 ng/mL, respectively.

Effect of Renal Impairment

Anastrozole pharmacokinetics have been investigated in subjects with renal impairment. Anastrozole renal clearance decreased proportionally with creatinine clearance and was approximately 50% lower in volunteers with severe renal impairment (creatinine clearance < 30 mL/min/1.73m^2) compared to controls. Total clearance was only reduced 10%. No dosage adjustment is needed for renal impairment [see Dosage and Administration (2.1) and Use in Specific Populations (8.6)].

Effect of Hepatic Impairment

Anastrozole pharmacokinetics have been investigated in subjects with hepatic cirrhosis related to alcohol abuse. The apparent oral clearance (CL/F) of anastrozole was approximately 30% lower in subjects with stable hepatic cirrhosis than in control subjects with normal liver function. However, these plasma concentrations were still with the range of values observed in normal subjects. The effect of severe hepatic impairment was not studied. No dose adjustment is necessary for stable hepatic cirrhosis [see Dosage and Administration (2.2) and Use in Specific Populations (8.7)].

13 NONCLINICAL TOXICOLOGY

13.1 Carcinogenesis, Mutagenesis, Impairment of Fertility

A conventional carcinogenesis study in rats at doses of 1.0 to 25 mg/kg/day (about 10 to 243 times the daily maximum recommended human dose on a mg/m^2 basis) administered by oral gavage for up to 2 years revealed an increase in the incidence of hepatocellular adenoma and carcinoma and uterine stromal polyps in females and thyroid adenoma in males at the high dose. A dose-related increase was observed in the incidence of ovarian and uterine hyperplasia in females. At 25 mg/kg/day, plasma AUC0-24 hr levels in rats were 110 to 125 times higher than the level exhibited in postmenopausal volunteers at the recommended dose. A separate carcinogenicity study in mice at oral doses of 5 to 50 mg/kg/day (about 24 to 243 times the daily maximum recommended human dose on a mg/m^2 basis) for up to 2 years produced an increase in the incidence of benign ovarian stromal, epithelial and granulosa cell tumors at all dose levels. A dose-related increase in the incidence of ovarian hyperplasia was also observed in female mice. These ovarian changes are considered to be rodent-specific effects of aromatase inhibition and are of questionable significance to humans. The incidence of lymphosarcoma was increased in males and females at the high dose. At 50 mg/kg/day, plasma AUC levels in mice were 35 to 40 times higher than the level exhibited in postmenopausal volunteers at the recommended dose.

ARIMIDEX has not been shown to be mutagenic in in vitro tests (Ames and E. coli bacterial tests, CHO-K1 gene mutation assay) or clastogenic either in vitro (chromosome aberrations in human lymphocytes) or in vivo (micronucleus test in rats).

Oral administration of anastrozole to female rats (from 2 weeks before mating to pregnancy day 7) produced significant incidence of infertility and reduced numbers of viable pregnancies at 1 mg/kg/day (about 10 times the recommended human dose on a mg/m^2 basis and 9 times higher than the AUC0-24 hr found in postmenopausal volunteers at the recommended dose). Pre-implantation loss of ova or fetus was increased at doses equal to or greater than 0.02 mg/kg/day (about one-fifth the recommended human dose on a mg/m^2 basis). Recovery of fertility was observed following a 5-week non-dosing period which followed 3 weeks of dosing. It is not known whether these effects observed in female rats are indicative of impaired fertility in humans.

Multiple-dose studies in rats administered anastrozole for 6 months at doses equal to or greater than 1 mg/kg/day (which produced plasma anastrozole Cssmax and AUC0-24 hr that were 19 and 9 times higher than the respective values found in postmenopausal volunteers at the recommended dose) resulted in hypertrophy of the ovaries and the presence of follicular cysts. In addition, hyperplastic uteri were observed in 6-month studies in female dogs administered doses equal to or greater than 1 mg/kg/day (which produced plasma anastrozole Cssmax and AUC0-24 hr that were 22 times and 16 times higher than the respective values found in postmenopausal women at the recommended dose). It is not known whether these effects on the reproductive organs of animals are associated with impaired fertility in premenopausal women.

14 CLINICAL STUDIES

14.1 Adjuvant Treatment of Breast Cancer in Postmenopausal Women

A multicenter, double-blind trial (ATAC) randomized 9,366 postmenopausal women with operable breast cancer to adjuvant treatment with ARIMIDEX 1 mg daily, tamoxifen 20 mg daily, or a combination of the two treatments for five years or until recurrence of the disease.

The primary endpoint of the trial was disease-free survival (i.e., time to occurrence of a distant or local recurrence, or contralateral breast cancer or death from any cause). Secondary endpoints of the trial included distant disease-free survival, the incidence of contralateral breast cancer and overall survival. At a median follow-up of 33 months, the combination of ARIMIDEX and tamoxifen did not demonstrate any efficacy benefit when compared with tamoxifen in all patients as well as in the hormone receptor positive subpopulation. This treatment arm was discontinued from the trial. Based on clinical and pharmacokinetic results from the ATAC trial, tamoxifen should not be administered with anastrozole [see Drug Interactions (7.1)].

Demographic and other baseline characteristics were similar among the three treatment groups (see Table 7).

Table 7 - Demographic and Baseline Characteristics for ATAC Trial
Demographic Characteristic | ARIMIDEX 1 mg (N [N=Number of patients randomized to the treatment] =3125) | Tamoxifen 20 mg (N=3116) | ARIMIDEX 1 mg plus Tamoxifen [The combination arm was discontinued due to lack of efficacy benefit at 33 months of follow-up] 20 mg (N=3125)
Mean age (yrs.) | 64.1 | 64.1 | 64.3
Age Range (yrs.) | 38.1 - 92.8 | 32.8 - 94.9 | 37.0 - 92.2
Age Distribution (%)
<45 yrs. | 0.7 | 0.4 | 0.5
45-60 yrs. | 34.6 | 35.0 | 34.5
>60 <70 yrs. | 38.0 | 37.1 | 37.7
>70 yrs. | 26.7 | 27.4 | 27.3
Mean Weight (kg) | 70.8 | 71.1 | 71.3
Receptor Status (%)
Positive [Includes patients who were estrogen receptor (ER) positive or progesterone receptor (PgR) positive, or both positive] | 83.5 | 83.1 | 84.0
Negative [Includes patients with both ER negative and PgR negative receptor status] | 7.4 | 8.0 | 7.0
Other [Includes all other combinations of ER and PgR receptor status unknown] | 8.8 | 8.6 | 9.0
Other Treatment (%) prior to Randomization
Mastectomy | 47.8 | 47.3 | 48.1
Breast conservation [Among the patients who had breast conservation, radiotherapy was administered to 95.0% of patients in the ARIMIDEX arm, 94.1% in the tamoxifen arm and 94.5% in the ARIMIDEX plus tamoxifen arm.] | 52.3 | 52.8 | 51.9
Axillary surgery | 95.5 | 95.7 | 95.2
Radiotherapy | 63.3 | 62.5 | 61.9
Chemotherapy | 22.3 | 20.8 | 20.8
Neoadjuvant Tamoxifen | 1.6 | 1.6 | 1.7
Primary Tumor Size (%)
T1 (≤2 cm) | 63.9 | 62.9 | 64.1
T2 (>2 cm and ≤5 cm) | 32.6 | 34.2 | 32.9
T3 (>5 cm) | 2.7 | 2.2 | 2.3
Nodal Status (%)
Node positive | 34.9 | 33.6 | 33.5
1-3 (# of nodes) | 24.4 | 24.4 | 24.3
4-9 | 7.5 | 6.4 | 6.8
>9 | 2.9 | 2.7 | 2.3
Tumor Grade (%)
Well-differentiated | 20.8 | 20.5 | 21.2
Moderately differentiated | 46.8 | 47.8 | 46.5
Poorly/undifferentiated | 23.7 | 23.3 | 23.7
Not assessed/recorded | 8.7 | 8.4 | 8.5

Patients in the two monotherapy arms of the ATAC trial were treated for a median of 60 months (5 years) and followed for a median of 68 months. Disease-free survival in the intent-to-treat population was statistically significantly improved [Hazard Ratio (HR) = 0.87, 95% CI: 0.78, 0.97, p=0.0127] in the ARIMIDEX arm compared to the tamoxifen arm. In the hormone receptor-positive subpopulation representing about 84% of the trial patients, disease-free survival was also statistically significantly improved (HR = 0.83, 95% CI: 0.73, 0.94, p=0.0049) in the ARIMIDEX arm compared to the tamoxifen arm.

Figure 1 - Disease-Free Survival Kaplan Meier Survival Curve for all Patients Randomized to ARIMIDEX or Tamoxifen Monotherapy in the ATAC Trial (Intent-to-Treat)

Figure 2 - Disease-Free Survival for Hormone Receptor-Positive Subpopulation of Patients Randomized to ARIMIDEX or Tamoxifen Monotherapy in the ATAC Trial

The survival data with 68 months follow-up is presented in Table 9.

In the group of patients who had previous adjuvant chemotherapy (N=698 for ARIMIDEX and N=647 for tamoxifen), the hazard ratio for disease-free survival was 0.91 (95% CI: 0.73 to 1.13) in the ARIMIDEX arm compared to the tamoxifen arm.

The frequency of individual events in the intent-to-treat population and the hormone receptor-positive subpopulation are described in Table 8.

Table 8 - All Recurrence and Death Events [The combination arm was discontinued due to lack of efficacy benefit at 33 months of follow-up.]
 | Intent-To-Treat Population [Patients may fall into more than one category.] |  | Hormone Receptor-Positive Subpopulation
 | ARIMIDEX 1 mg (N [N=Number of patients randomized.] =3125) | Tamoxifen 20 mg (N=3116) | ARIMIDEX 1 mg (N=2618) | Tamoxifen 20 mg (N=2598)
Median Duration of Therapy (mo) | 60 | 60 | 60 | 60
Median Efficacy Follow-up (mo) | 68 | 68 | 68 | 68
Loco-regional recurrence | 119 (3.8) | 149 (4.8) | 76 (2.9) | 101 (3.9)
Contralateral breast cancer | 35 (1.1) | 59 (1.9) | 26 (1.0) | 54 (2.1)
Invasive | 27 (0.9) | 52 (1.7) | 21 (0.8) | 48 (1.8)
Ductal carcinoma in situ | 8 (0.3) | 6 (0.2) | 5 (0.2) | 5 (0.2)
Unknown | 0 | 1 (<0.1) | 0 | 1 (<0.1)
Distant recurrence | 324 (10.4) | 375 (12.0) | 226 (8.6) | 265 (10.2)
Death from Any Cause | 411 (13.2) | 420 (13.5) | 296 (11.3) | 301 (11.6)
Death breast cancer | 218 (7.0) | 248 (8.0) | 138 (5.3) | 160 (6.2)
Death other reason (including unknown) | 193 (6.2) | 172 (5.5) | 158 (6.0) | 141 (5.4)

A summary of the study efficacy results is provided in Table 9.

Table 9 - ATAC Efficacy Summary [The combination arm was discontinued due to lack of efficacy benefit at 33 months of follow-up.]
 | Intent-To-Treat Population |  | Hormone Receptor-Positive Subpopulation
 | ARIMIDEX 1 mg; (N=3125) | Tamoxifen 20 mg; (N=3116) | ARIMIDEX 1 mg; (N=2618) | Tamoxifen 20 mg; (N=2598)
 | Number of Events |  | Number of Events
Disease-free Survival | 575 | 651 | 424 | 497
Hazard ratio | 0.87 |  | 0.83
2-sided 95% CI | 0.78 to 0.97 |  | 0.73 to 0.94
p-value | 0.0127 |  | 0.0049
Distant Disease-free Survival | 500 | 530 | 370 | 394
Hazard ratio | 0.94 |  | 0.93
2-sided 95% CI | 0.83 to 1.06 |  | 0.80 to 1.07
Overall Survival | 411 | 420 | 296 | 301
Hazard ratio | 0.97 |  | 0.97
2-sided 95% CI | 0.85 to 1.12 |  | 0.83 to 1.14

10-year median follow-up Efficacy Results from the ATAC Trial

In a subsequent analysis of the ATAC trial, patients in the two monotherapy arms were followed for a median of 120 months (10 years). Patients received study treatment for a median of 60 months (5 years) (see Table 10).

Table 10 - Efficacy Summary
 | Intent-To-Treat Population |  | Hormone Receptor-Positive Subpopulation
 | ARIMIDEX 1 mg; (N=3125) | Tamoxifen 20 mg; (N=3116) | ARIMIDEX 1 mg; (N=2618) | Tamoxifen 20 mg; (N=2598)
 | Number of Events |  | Number of Events
Disease-free Survival | 953 | 1022 | 735 | 924
Hazard ratio | 0.91 |  | 0.86
2-sided 95% CI | 0.83 to 0.99 |  | 0.78 to 0.95
p-value | 0.0365 |  | 0.0027
Overall Survival | 734 | 747 | 563 | 586
Hazard ratio | 0.97 |  | 0.95
2-sided 95% CI | 0.88 to 1.08 |  | 0.84 to 1.06

Figure 3 - Disease-Free Survival Kaplan Meier Survival Curve for all Patients Randomized to ARIMIDEX or Tamoxifen Monotherapy in the ATAC Trial (Intent-to-Treat)(a)

a The proportion of patients with 120 months’ follow-up was 29.4%.

Figure 4 - Disease-Free Survival for Hormone Receptor-Positive Subpopulation of Patients Randomized to ARIMIDEX or Tamoxifen Monotherapy in the ATAC Trial(b)

b The proportion of patients with 120 months’ follow-up was 29.8%.

14.2 First-Line Therapy in Postmenopausal Women with Advanced Breast Cancer

Two double-blind, controlled clinical studies of similar design (0030, a North American study and 0027, a predominately European study) were conducted to assess the efficacy of ARIMIDEX compared with tamoxifen as first-line therapy for hormone receptor positive or hormone receptor unknown locally advanced or metastatic breast cancer in postmenopausal women. A total of 1021 patients between the ages of 30 and 92 years old were randomized to receive trial treatment. Patients were randomized to receive 1 mg of ARIMIDEX once daily or 20 mg of tamoxifen once daily. The primary endpoints for both trials were time to tumor progression, objective tumor response rate, and safety.

Demographics and other baseline characteristics, including patients who had measurable and no measurable disease, patients who were given previous adjuvant therapy, the site of metastatic disease and ethnic origin were similar for the two treatment groups for both trials. The following table summarizes the hormone receptor status at entry for all randomized patients in trials 0030 and 0027.

Table 11 - Demographic and Other Baseline Characteristics
 | Number (%) of subjects
 | Trial 0030 |  | Trial 0027
Receptor status | ARIMIDEX 1 mg (N=171) | Tamoxifen 20 mg (N=182) | ARIMIDEX 1 mg (N=340) | Tamoxifen 20 mg (N=328)
ER [ER=Estrogen receptor] and/or PgR [PgR=Progesterone receptor] | 151 (88.3) | 162 (89.0) | 154 (45.3) | 144 (43.9)
ER unknown, PgR unknown | 19 (11.1) | 20 (11.0) | 185 (54.4) | 183 (55.8)

For the primary endpoints, trial 0030 showed that ARIMIDEX had a statistically significant advantage over tamoxifen (p=0.006) for time to tumor progression; objective tumor response rates were similar for ARIMIDEX and tamoxifen. Trial 0027 showed that ARIMIDEX and tamoxifen had similar objective tumor response rates and time to tumor progression (see Table 12 and Figures 5 and 6).

Table 12 below summarizes the results of trial 0030 and trial 0027 for the primary efficacy endpoints.

Table 12 - Efficacy Results of First-line Treatment
Endpoint | Trial 0030 |  | Trial 0027
 | ARIMIDEX 1 mg (N=171) | Tamoxifen 20 mg (N=182) | ARIMIDEX 1 mg (N=340) | Tamoxifen 20 mg (N=328)
Time to progression (TTP)
Median TTP (months) | 11.1 | 5.6 | 8.2 | 8.3
Number (%) of subjects who progressed | 114 (67%) | 138 (76%) | 249 (73%) | 247 (75%)
Hazard ratio (LCL [LCL=Lower Confidence Limit]) [Tamoxifen:ARIMIDEX] | 1.42 (1.15) |  | 1.01 (0.87)
2-sided 95% CI [CI=Confidence Interval] | (1.11, 1.82) |  | (0.85, 1.20)
p-value [Two-sided Log Rank] | 0.006 |  | 0.920
Best objective response rate
Number (%) of subjects with CR [CR=Complete Response] + PR [PR=Partial Response] | 36 (21.1%) | 31 (17.0%) | 112 (32.9%) | 107 (32.6%)
Odds Ratio (LCL) [ARIMIDEX:Tamoxifen] | 1.30 (0.83) |  | 1.01 (0.77)

Figure 5 - Kaplan-Meier probability of time to disease progression for all randomized patients (intent-to-treat) in Trial 0030

Figure 6 - Kaplan-Meier probability of time to progression for all randomized patients (intent-to-treat) in Trial 0027

Results from the secondary endpoints were supportive of the results of the primary efficacy endpoints. There were too few deaths occurring across treatment groups of both trials to draw conclusions on overall survival differences.

14.3 Second-Line Therapy in Postmenopausal Women with Advanced Breast Cancer who had Disease Progression following Tamoxifen Therapy

Anastrozole was studied in two controlled clinical trials (0004, a North American study; 0005, a predominately European study) in postmenopausal women with advanced breast cancer who had disease progression following tamoxifen therapy for either advanced or early breast cancer. Some of the patients had also received previous cytotoxic treatment. Most patients were ER-positive; a smaller fraction were ER-unknown or ER-negative; the ER-negative patients were eligible only if they had a positive response to tamoxifen. Eligible patients with measurable and non-measurable disease were randomized to receive either a single daily dose of 1 mg or 10 mg of ARIMIDEX or megestrol acetate 40 mg four times a day. The studies were double-blinded with respect to ARIMIDEX. Time to progression and objective response (only patients with measurable disease could be considered partial responders) rates were the primary efficacy variables. Objective response rates were calculated based on the Union Internationale Contre le Cancer (UICC) criteria. The rate of prolonged (more than 24 weeks) stable disease, the rate of progression, and survival were also calculated.

Both trials included over 375 patients; demographics and other baseline characteristics were similar for the three treatment groups in each trial. Patients in the 0005 trial had responded better to prior tamoxifen treatment. Of the patients entered who had prior tamoxifen therapy for advanced disease (58% in Trial 0004; 57% in Trial 0005), 18% of these patients in Trial 0004 and 42% in Trial 0005 were reported by the primary investigator to have responded. In Trial 0004, 81% of patients were ER-positive, 13% were ER-unknown, and 6% were ER-negative. In Trial 0005, 58% of patients were ER-positive, 37% were ER-unknown, and 5% were ER-negative. In Trial 0004, 62% of patients had measurable disease compared to 79% in Trial 0005. The sites of metastatic disease were similar among treatment groups for each trial. On average, 40% of the patients had soft tissue metastases; 60% had bone metastases; and 40% had visceral (15% liver) metastases.

Efficacy results from the two studies were similar as presented in Table 13. In both studies there were no significant differences between treatment arms with respect to any of the efficacy parameters listed in the table below.

Table 13 - Efficacy Results of Second-line Treatment
 | ARIMIDEX 1 mg | ARIMIDEX 10 mg | Megestrol Acetate 160 mg
Trial 0004
(N. America) | (N=128) | (N=130) | (N=128)
Median Follow-up (months) [Surviving Patients] | 31.3 | 30.9 | 32.9
Median Time to Death (months) | 29.6 | 25.7 | 26.7
2 Year Survival Probability (%) | 62.0 | 58.0 | 53.1
Median Time to Progression (months) | 5.7 | 5.3 | 5.1
Objective Response (all patients) (%) | 12.5 | 10.0 | 10.2
Stable Disease for >24 weeks (%) | 35.2 | 29.2 | 32.8
Progression (%) | 86.7 | 85.4 | 90.6
Trial 0005
(Europe, Australia, S. Africa) | (N=135) | (N=118) | (N=125)
Median Follow-up (months) | 31.0 | 30.9 | 31.5
Median Time to Death (months) | 24.3 | 24.8 | 19.8
2 Year Survival Probability (%) | 50.5 | 50.9 | 39.1
Median Time to Progression (months) | 4.4 | 5.3 | 3.9
Objective Response (all patients) (%) | 12.6 | 15.3 | 14.4
Stable Disease for >24 weeks (%) | 24.4 | 25.4 | 23.2
Progression (%) | 91.9 | 89.8 | 92.0

When data from the two controlled trials are pooled, the objective response rates and median times to progression and death were similar for patients randomized to ARIMIDEX 1 mg and megestrol acetate. There is, in this data, no indication that ARIMIDEX 10 mg is superior to ARIMIDEX 1 mg.

Table 14 - Pooled Efficacy Results of Second-line Treatment
Trials 0004 & 0005 (Pooled Data) | ARIMIDEX 1 mg N=263 | ARIMIDEX 10 mg N=248 | Megestrol Acetate 160 mg N=253
Median Time to Death (months) | 26.7 | 25.5 | 22.5
2 Year Survival Probability (%) | 56.1 | 54.6 | 46.3
Median Time to Progression | 4.8 | 5.3 | 4.6
Objective Response (all patients) (%) | 12.5 | 12.5 | 12.3

16 HOW SUPPLIED/STORAGE AND HANDLING

ARIMIDEX (anastrozole) Tablets, 1 mg are supplied in bottles of 30 tablets (NDC 62559-670-30).

Storage
Store at controlled room temperature, 20 to 25°C (68 to 77°F) [see USP].

17 PATIENT COUNSELING INFORMATION

See FDA approved patient labeling (Patient Information).

Hypersensitivity Reactions

Inform patients of the possibility of serious allergic reactions with swelling of the face, lips, tongue and/or throat (angioedema) which may cause difficulty in swallowing and/or breathing and to seek medical attention immediately [see Contraindications (4)].

Ischemic Cardiovascular Events

Patients with pre-existing ischemic heart disease should be informed that an increased incidence of cardiovascular events has been observed with ARIMIDEX use compared to tamoxifen use. Advise patients if new or worsening chest pain or shortness of breath occurs to seek medical attention immediately [see Warnings and Precautions (5.1)].

Bone Effects

Inform patients that ARIMIDEX lowers the level of estrogen. This may lead to a loss of the mineral content of bones, which might decrease bone strength. A possible consequence of decreased mineral content of bones is an increase in the risk of fractures [see Warnings and Precautions (5.2)].

Cholesterol

Inform patients that an increased level of cholesterol might be seen while receiving ARIMIDEX [see Warnings and Precautions (5.3)].

Carpal Tunnel

Patients should be informed that if they experience tickling, tingling, or numbness they should notify their health care provider [see Adverse Reactions (6.1)].

Tamoxifen

Patients should be advised not to take ARIMIDEX with Tamoxifen [see Clinical Studies (14.1)].

Missed Doses

Inform patients that if they miss a dose, take it as soon as they remember. If it is almost time for their next dose, skip the missed dose and take the next regularly scheduled dose. Patients should not take two doses at the same time.

Embryo-Fetal Toxicity

Advise females of reproductive potential of the potential risk to a fetus and to use effective contraception during ARIMIDEX therapy and for at least 3 weeks after the last dose. Advise females to contact their healthcare provider if they become pregnant, or if pregnancy is suspected, during treatment with ARMIDEX [see Warning and Precautions (5.4) and Use in Specific Populations (8.1, 8.3)].

Lactation

Advise women not to breastfeed during ARIMIDEX treatment and for at least 2 weeks after the last dose [see Use in Specific Population (8.2)].

Distributed by:
ANI Pharmaceuticals, Inc.
Baudette, MN 56623

ARIMIDEX is a registered trademark of the AstraZeneca group of companies and is licensed to ANI Pharmaceuticals, Inc.

Patient Information

ARIMIDEX®
A-rim-eh-dex
(anastrozole)
tablets

What is the most important information I should know about ARIMIDEX?

ARIMIDEX may cause serious side effects including:

- heart disease. Women with early breast cancer, who have a history of blockage in their heart arteries (ischemic heart disease) and who take ARIMIDEX, may have an increase in symptoms of decreased blood flow to their heart compared to similar women who take tamoxifen.
  Get medical help right away if you have new or worsening chest pain or shortness of breath during treatment with ARIMIDEX.

What is ARIMIDEX?

ARIMIDEX is a prescription medicine used in women after menopause (“the change of life”) for:

- treatment of early breast cancer
- after surgery
- in women whose breast cancer is hormone receptor-positive
- the first treatment of breast cancer that has spread to nearby tissue or lymph nodes (locally advanced) or has spread to other parts of the body (metastatic), in women whose breast cancer is hormone receptor-positive or the hormone receptors are not known
- treatment of advanced breast cancer, if the cancer has grown, or the disease has spread after tamoxifen therapy

ARIMIDEX does not work in women with breast cancer who have not gone through menopause (premenopausal women).

Who should not take ARIMIDEX?

Do not take ARIMIDEX if you:

- have had a severe allergic reaction to anastrozole or any of the ingredients in ARIMIDEX. See the end of this leaflet for a complete list of ingredients in ARIMIDEX. Symptoms of a severe allergic reaction to ARIMIDEX include: swelling of the face, lips, tongue, or throat, trouble breathing or swallowing, hives and itching.

What should I tell my healthcare provider before taking ARIMIDEX?

Before you take ARIMIDEX, tell your healthcare provider if you:

- are still having menstrual periods (are not past menopause). Talk to your healthcare provider if you are not sure.
- have or had a heart problem
- have been told you have bone thinning or weakness (osteoporosis)
- have high cholesterol
- have any other medical conditions
- are pregnant or plan to become pregnant. Taking ARIMIDEX during pregnancy or within 3 weeks of becoming pregnant may harm your unborn baby.
- Females who are able to become pregnant should have a pregnancy test before starting treatment with ARIMIDEX.
- Females who are able to become pregnant should use effective birth control (contraceptive) during treatment with ARIMIDEX and for 3 weeks after your last dose of ARIMIDEX. Tell your healthcare provider right away if you become pregnant or think you may be pregnant.
- are breastfeeding or plan to breastfeed. It is not known if ARIMIDEX passes into breast milk. Do not breastfeed during treatment with ARIMIDEX and for 2 weeks after your last dose of ARIMIDEX.

Tell your healthcare provider about all the medicines you take, including prescription and over-the-counter medicines, vitamins, and herbal supplements. Especially tell your healthcare provider if you take:

- tamoxifen. You should not take ARIMIDEX if you take tamoxifen. Taking ARIMIDEX with tamoxifen may lower the amount of ARIMIDEX in your blood and may cause ARIMIDEX not to work as well.
- Medicines that contain estrogen. ARIMIDEX may not work if taken with any of these medicines:
- hormone replacement therapy
- birth control pills
- estrogen creams
- vaginal rings
- vaginal suppositories

Know the medicines you take. Keep a list of them to show your healthcare provider and pharmacist when you get a new medicine.

How should I take ARIMIDEX?

- Take ARIMIDEX exactly as your healthcare provider tells you to take it.
- Continue taking ARIMIDEX until your healthcare provider tells you to stop.
- ARIMIDEX can be taken with or without food.
- If you miss a dose, take it as soon as you remember. If it is almost time for your next dose, skip the missed dose. Take your next regularly scheduled dose. Do not take two doses at the same time.

If you take too much ARIMIDEX, call your healthcare provider or go to the nearest hospital emergency room right away.

What are the possible side effects of ARIMIDEX?

ARIMIDEX may cause serious side effects including:

- See “What is the most important information I should know about ARIMIDEX?”
- bone thinning or weakness (osteoporosis). ARIMIDEX lowers estrogen in your body, which may cause your bones to become thinner and weaker. This may increase your risk of fractures, especially of your spine, hip and wrist. Your healthcare provider may order a bone mineral density test before you start and during treatment with ARIMIDEX to check you for bone changes.
- increased blood cholesterol (fat in the blood). Your healthcare provider may do blood tests to check your cholesterol while you are taking ARIMIDEX.
- skin reactions. Stop taking ARIMIDEX and call your healthcare provider right away if you get any skin lesions, ulcers, or blisters.
- severe allergic reactions. Get medical help right away if you get:
- swelling of your face, lips, tongue, or throat
- trouble swallowing or breathing

- liver problems. ARIMIDEX can cause inflammation of your liver and changes in liver function blood tests. Your healthcare provider may check you for this.
  Stop taking ARIMIDEX and call your healthcare provider right away if you have any of these signs or symptoms of a liver problem:
- a general feeling of not being well
- yellowing of your skin or whites of your eyes
- pain on the right side of your stomach-area (abdomen)

Common side effects in women taking ARIMIDEX include:

- hot flashes
- weakness
- joint aches
- joint pain, stiffness or swelling (arthritis)
- pain
- sore throat
- high blood pressure
- depression
- nausea and vomiting
- rash
- back pain
- sleep problems
- bone pain
- headache
- swelling of your legs, ankles, or feet
- increased cough
- shortness of breath
- build up of lymph fluid in the tissues of your affected arm (lymphedema)

ARIMIDEX may also cause you to have tickling, tingling or numbness of your skin.

Tell your healthcare provider if you have any side effect that bothers you or that does not go away.

These are not all the possible side effects of ARIMIDEX. For more information, ask your healthcare provider or pharmacist.

Call your healthcare provider for medical advice about side effects. You may report side effects to FDA at 1-800-FDA-1088.

How should I store ARIMIDEX?

- Store ARIMIDEX at room temperature between 68°F to 77°F (20°C to 25°C).

Keep ARIMIDEX and all medicines out of the reach of children.

General information about the safe and effective use of ARIMIDEX.

Medicines are sometimes prescribed for purposes other than those listed in a Patient Information leaflet. Do not take ARIMIDEX for a condition for which it was not prescribed. Do not give ARIMIDEX to other people, even if they have the same symptoms that you have. It may harm them.

If you would like more information, talk with your healthcare provider. You can ask your pharmacist or healthcare provider for information about ARIMIDEX that is written for health professionals. For more information call 1-800-308-6755 or go to www.ARIMIDEX.com.

What are the ingredients in ARIMIDEX?

Active ingredient: anastrozole

Inactive ingredients: lactose, magnesium stearate, hypromellose, polyethylene glycol, povidone, sodium starch glycolate, and titanium dioxide.

This Patient Information has been approved by the U.S. Food and Drug Administration.

Revised: December 2018

Distributed by:
ANI Pharmaceuticals, Inc.
Baudette, MN 56623

ARIMIDEX is a registered trademark of the AstraZeneca group of companies and is licensed to ANI Pharmaceuticals, Inc.

PACKAGE/LABEL PRINCIPAL DISPLAY PANEL

Arimidex®
anastrozole tablets
1 mg
NDC 62559-670-30
Rx only
30 Tablets